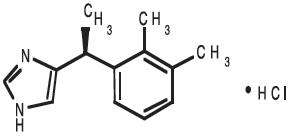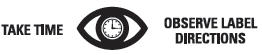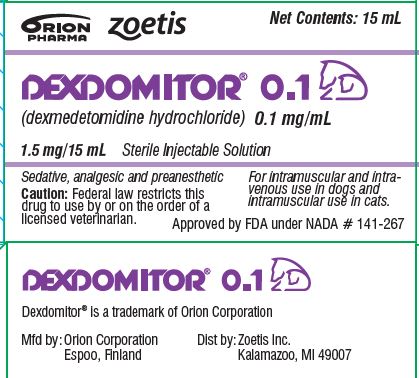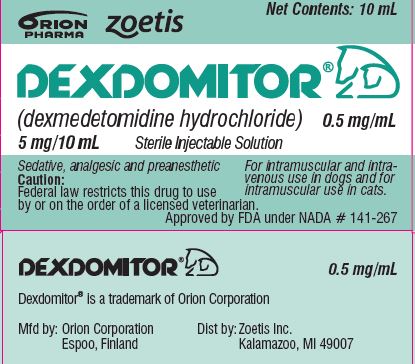 DRUG LABEL: Dexdomitor
NDC: 54771-2805 | Form: INJECTION, SOLUTION
Manufacturer: Zoetis Inc.
Category: animal | Type: PRESCRIPTION ANIMAL DRUG LABEL
Date: 20230706

ACTIVE INGREDIENTS: dexmedetomidine hydrochloride 0.5 mg/1 mL
INACTIVE INGREDIENTS: methylparaben 1.6 mg/1 mL; propylparaben 0.2 mg/1 mL; sodium chloride 9 mg/1 mL; water

DEXDOMITOR®

Sterile Injectable Solution – 0.1 mg/mL
Intramuscular and Intravenous use in Dogs
Intramuscular use in Cats
Sedative, Analgesic, Preanesthetic

CAUTION

Federal law restricts this drug to use by or on the order of a licensed veterinarian.

DESCRIPTION

DEXDOMITOR (dexmedetomidine hydrochloride) is a synthetic alpha2-adrenoreceptor agonist with sedative and analgesic properties. The chemical name is (+)-4-[1-(2,3-dimethylphenyl) ethyl]-1H-imidazole monohydrochloride. It is a white, or almost white, crystalline, water soluble substance having a molecular weight of 236.7. The molecular formula is C13 H16 N2 ∙HCl and the structural formula is:

0.1 - Each mL of DEXDOMITOR contains 0.5 mg dexmedetomidine hydrochloride, 1.6 mg methylparaben (NF), 0.2 mg propylparaben (NF), 9.0 mg sodium chloride (USP), and water for injection (USP), q.s.

INDICATIONS

DEXDOMITOR is indicated for use as a sedative and analgesic in dogs and cats to facilitate clinical examinations, clinical procedures, minor surgical procedures, and minor dental procedures. DEXDOMITOR is also indicated for use as a preanesthetic to general anesthesia in dogs and cats.

DOSAGE AND ADMINISTRATION

Dogs - 0.1

Sedation and Analgesia: 500 mcg/m^2 intramuscularly (IM) or 375 mcg/m^2 intravenously (IV). Preanesthesia: 125 or 375 mcg/m^2 IM.

The choice of preanesthetic dose depends on the duration and severity of the procedure, as well as the anesthetic regime. The following two tables may be used to determine the correct dexmedetomidine dosage. Note that the mcg/kg dosage decreases as body weight increases. For example, dogs weighing 2 kg are dosed at 28.1 mcg/kg dexmedetomidine IV, compared to dogs weighing 80 kg that are dosed at 8.7 mcg/kg. Due to the small volume of administration, accurate dosing is not possible in dogs weighing less than 2 kg (4.4 lb).

Table 1: CANINE SEDATION/ANALGESIA DOSE TABLE: Intravenous (IV) and intramuscular (IM) dosing on the basis of body weight.
DEXDOMITOR 0.1 mg/mL
Sedation/analgesia in dogs
Dog Weight |  | Dexmedetomidine 375 mcg/m^2IV |  | Dexmedetomidine 500 mcg/m^2IM
lbs | Kg | mcg/kg | mL | mcg/kg | mL
4.4-7 | 2-3 | 28.1 | 0.6 | 40 | 0.75
7.1-9 | 3.1-4 | 25 | 0.75 | 35 | 1
9.1-11 | 4.1-5 | 23 | 1 | 30 | 1.5
11.1-22 | 5.1-10 | 19.6 | 1.45 | 25 | 2
22.1-29 | 10.1-13 | 16.8 | 1.9

Table 2: CANINE PREANESTHESIA DOSE TABLE: Intramuscular (IM) dosing on the basis of body weight.
DEXDOMITOR 0.1 mg/mL
Preanesthesia in dogs
Dog Weight |  | Dexmedetomidine 125 mcg/m^2IM |  | Dexmedetomidine 375 mcg/m^2IM
lbs | Kg | mcg/kg | mL | mcg/kg | mL
4.4-7 | 2-3 | 9.4 | 0.2 | 28.1 | 0.6
7.1-9 | 3.1-4 | 8.3 | 0.25 | 25 | 0.75
9.1-11 | 4.1-5 | 7.7 | 0.35 | 23 | 1
11.1-22 | 5.1-10 | 6.5 | 0.5 | 19.6 | 1.45
22.1-29 | 10.1-13 | 5.6 | 0.65 | 16.8 | 1.9
29.1-33 | 13.1-15 | 5.2 | 0.75
33.1-44 | 15.1-20 | 4.9 | 0.85

For higher weight ranges, use DEXDOMITOR’s higher concentration and its associated dosing chart.

The use of dexmedetomidine as a preanesthetic markedly reduces anesthetic requirements in dogs. Injectable induction drug requirements for intubation will be reduced between 30% and 60%, depending on the choice of anesthetic and the dexmedetomidine preanesthetic dose. The concentration of inhalation maintenance anesthetic will be reduced between 40% and 60%, depending on the dose of dexmedetomidine. The anesthetic dose should always be titrated against the response of the patient. The choice of anesthetic is left to the discretion of the veterinarian.

Cats - 0.1

Sedation, Analgesia and Preanesthesia: 40 mcg/kg intramuscularly (IM).

This dose can also be used as a preanesthetic and has been shown to markedly reduce anesthetic requirements in cats. Injectable anesthetic drug requirements for intubation were reduced up to 49%, depending on the choice of induction drug. The concentration of inhalation maintenance anesthetic was reduced between 35% and 44%, depending on the choice of induction drug. The anesthetic dose should always be titrated against the response of the patient.

The following table may be used to determine the correct dexmedetomidine dosage for cats based on body weight.

Table 3: FELINE DOSE TABLE: Intramuscular (IM) dosing on the basis of body weight in cats.

DEXDOMITOR 0.1 mg/mL
Sedation/analgesia and preanesthesia in cats
Cat Weight |  | Dexmedetomidine 40 mcg/kg IM
lbs | kg | mcg/kg | mL
2-4 | 1-2 | 40 | 0.5
4.1-7 | 2.1-3 | 40 | 1

For higher weight ranges, use DEXDOMITOR’s higher concentration and its associated dosing chart.

It is recommended that dogs and cats be fasted for 12 hours before treatment with DEXDOMITOR. An eye lubricant should be applied to cats to prevent corneal desiccation that may result from a reduction in the blink reflex. Following injection of DEXDOMITOR, the animal should be allowed to rest quietly for 15 minutes; sedation and analgesia occur within 5 to 15 minutes, with peak effects at 30 minutes after dexmedetomidine.

CONTRAINDICATIONS

Do not use DEXDOMITOR in dogs or cats with cardiovascular disease, respiratory disorders, liver or kidney diseases, or in conditions of shock, severe debilitation, or stress due to extreme heat, cold or fatigue.

As with all alpha2-adrenoceptor agonists, the potential for isolated cases of hypersensitivity, including paradoxical response (excitation), exists.

WARNINGS

Human safety: Not for human use. Keep out of reach of children.
Dexmedetomidine hydrochloride can be absorbed following direct exposure to skin, eyes, or mouth, and may cause irritation. In case of accidental eye exposure, flush with water for 15 minutes. In case of accidental skin exposure, wash with soap and water. Remove contaminated clothing.
Appropriate precautions should be taken while handling and using filled syringes. Accidental topical (including ocular) exposure, oral exposure, or exposure by injection could cause adverse reactions, including sedation, hypotension, and bradycardia. Seek medical attention immediately.
Users with cardiovascular disease (for example, hypertension or ischemic heart disease) should take special precautions to avoid any exposure to this product.
Caution should be exercised when handling sedated animals. Handling or any other sudden stimuli, including noise, may cause a defense reaction in an animal that appears to be heavily sedated.
Note to physician: This product contains an alpha2-adrenergic agonist.
Animal safety: Dexmedetomidine should not be administered in the presence of preexisting hypotension, hypoxia, or bradycardia. Due to the pronounced cardiovascular effects of dexmedetomidine, only clinically healthy dogs and cats (ASA classes I and II) should be treated. Animals should be frequently monitored for cardiovascular function and body temperature during sedation or anesthesia. Dexmedetomidine sedation is not recommended for cats with respiratory disease.
The use of dexmedetomidine as a preanesthetic in dogs and cats significantly reduces the amount of induction and maintenance anesthetic requirements. Careful patient monitoring during anesthetic induction and maintenance is necessary to avoid anesthetic overdose.

CONTACT INFORMATION

For a copy of the Safety Data Sheet or to report adverse reactions, call Zoetis Inc. at 1-888-963-8471. For additional information about adverse drug experience reporting for animal drugs, contact FDA at 1-888-FDA-VETS or www.fda.gov/reportanimalae.

PRECAUTIONS

Apnea may occur with dexmedetomidine use. In the event of apnea, additional oxygen should be supplied. Administration of ANTISEDAN (atipamezole) to dogs is warranted when apnea is accompanied by bradycardia and cyanotic mucous membranes.
Adverse reaction reports for dexmedetomidine in cats include rare events of severe dyspnea and respiratory crackles diagnosed as acute pulmonary edema. Dyspnea due to the delayed onset of pulmonary edema could develop in rare instances up to three days after dexmedetomidine administration. Some of these acute and delayed pulmonary edema cases have resulted in death although this was not observed in the feline clinical field studies with dexmedetomidine.
In dogs, intramuscular ANTISEDAN (atipamezole) may be routinely used to rapidly reverse the effects of dexmedetomidine. Since analgesic as well as sedative effects will be reversed, pain management may need to be addressed.
In cats, ANTISEDAN (atipamezole) has not been evaluated as a routine dexmedetomidine reversal agent. In cats, cases of dyspnea following ANTISEDAN (atipamezole) administration have been reported.
Dexmedetomidine has not been evaluated in the presence of other preanesthetics in cats. Although not observed in the feline field studies, death has been reported in cats receiving dexmedetomidine in conjunction with ketamine and butorphanol.
Analgesia resulting from preanesthetic dexmedetomidine may not provide adequate pain control during the postoperative or postprocedural period. Additional pain management should be addressed as needed.
Following administration of dexmedetomidine, a decrease in body temperature is likely to occur unless externally maintained. Once established, hypothermia may persist longer than sedation and analgesia. To prevent hypothermia, treated animals should be kept warm and at a constant temperature during the procedure, and until full recovery.
Nervous or excited animals with high levels of endogenous catecholamines may exhibit a reduced pharmacological response to alpha2-adrenoceptor agonists like dexmedetomidine (ineffectiveness). In agitated animals, the onset of sedative/analgesic effects could be slowed, or the depth and duration of effects could be diminished or nonexistent. Therefore, allow dogs and cats to rest quietly for 10 to 15 minutes after injection. Repeat dosing has not been evaluated.
Administration of anticholinergic agents in dogs or cats at the same time or after dexmedetomidine could lead to adverse cardiovascular effects (secondary tachycardia, prolonged hypertension, and cardiac arrhythmias1, 2, 3). However, an anticholinergic drug may be administered to dogs at least 10 minutes before dexmedetomidine for the prevention of the dexmedetomidine-induced reduction in heart rate. Therefore, the routine use of anticholinergics simultaneously with, or after dexmedetomidine in dogs or cats, is not recommended (see ANIMAL SAFETY).
Spontaneous muscle contractions (twitching) can be expected in some dogs sedated with dexmedetomidine.
Dexmedetomidine has been evaluated only in fasted dogs; therefore, its effects on fed dogs (for example, the occurrence of vomiting) have not been characterized. In cats, there is a high frequency of vomition whether fed or fasted; therefore, fasting is recommended to reduce stomach contents.
Dexmedetomidine has not been evaluated in dogs younger than 16 weeks of age, in cats younger than 12 weeks of age, or in geriatric dogs and cats.
Dexmedetomidine has not been evaluated for use in breeding, pregnant, or lactating dogs or cats.

ADVERSE REACTIONS

Canine sedation/analgesia field study

In the field study safety analysis, 106 dogs received dexmedetomidine and 107 received medetomidine. Dogs ranged from 16 weeks to 16 years of age, representing 49 breeds. The following table shows the number of dogs displaying each clinical observation (some dogs experienced more than one adverse reaction).

Table 4: Adverse reactions during the canine sedation/analgesia field study
 | Dexmedetomidine Total n= 106 | Medetomidine Total n=107
Ausculted unidentified arrhythmias | 19 | 20
Severe bradycardia requiring treatment | 1 | 1
Apnea requiring treatment | 1 | 0
Slow onset of sedation (exceeding 30 minutes) | 1 | 1
Ineffectiveness (dog standing throughout the study) | 3 | 2
Severe hypothermia requiring treatment | 2 | 0
Prolonged recovery | 1 | 4

The occurrence of ausculted unidentified arrhythmias (some at multiple time points) decreased following the administration of atipamezole.

Canine preanesthesia field study

The preanesthesia field study safety analysis included 192 dogs, between 5 months and 15 years of age, representing 43 breeds enrolled for elective procedures conducted under general anesthesia. The following table shows the number of dogs within a treatment group that showed each clinical sign (dogs may have experienced more than one adverse reaction).

Table 5: Adverse reactions during the canine preanesthesia field study
 | Treatment Groups
Induction Anesthetic: | Propofol |  |  | Barbiturate
Preanesthetic Dose: | 0 mcg/m^2 n=32 | 125 mcg/m^2 n=32 | 375 mcg/m^2 n=32 | 0 mcg/m^2 n=32 | 125 mcg/m^2 n=32 | 375 mcg/m^2 n=32
Emesis | 4 | 7 | 4 | 2 | 3 | 6
Ventricular premature contractions | 0 | 2 | 0 | 4 | 1 | 0
Diarrhea | 1 | 0 | 0 | 3 | 1 | 1
Self trauma | 0 | 2 | 1 | 2 | 1 | 0
Severe bradycardia | 0 | 0 | 1 | 0 | 0 | 1
Tachycardia | 0 | 0 | 0 | 1 | 1 | 0
Urinary incontinence | 0 | 0 | 0 | 0 | 0 | 1

Other clinical signs observed in dogs treated with dexmedetomidine include decreased respiratory rate and hypothermia.

Feline sedation/analgesia field study

The field study safety analysis included 242 cats (122 received dexmedetomidine; 120 received xylazine), 6 months to 17 years of age, and representing 19 breeds. The following table shows the number of cats reported with an adverse reaction (cats may have experienced more than one adverse reaction).

Table 6: Adverse reactions during the feline field study
 | Dexmedetomidine n = 122 | Xylazine n = 120
Vomiting | 70 | 82
Urinary incontinence | 6 | 11
Hypersalivation | 4 | 5
Involuntary defecation | 4 | 1
Hypothermia | 2 | 1
Diarrhea | 2 | 0
Arrhythmia | 1 | 2
Corneal ulcer | 1 | 0
Cyanosis | 1 | 0
Dyspnea | 1 | 0

The most frequently observed adverse reaction was vomiting in both fasted and fed cats. Other infrequent clinical signs observed in cats treated with dexmedetomidine included fatigue, anorexia, cystitis, and peripheral vascular disorder.

One incidence of dyspnea was reported, 43 minutes after dexmedetomidine administration during an oral examination/dental procedure. Prior to dexmedetomidine, the cat was free of clinical signs, but had a history of asthma and respiratory infection. The cat responded successfully to treatment.

Feline preanesthesia field study

The field study safety analysis included 184 cats (116 received dexmedetomidine; 68 received saline), 12 weeks to 16 years of age, and representing 11 breeds. The following table shows the number of cats reported with an adverse reaction (cats may have experienced more than one adverse reaction).

Table 7. Adverse reactions during the feline preanesthesia field study
Induction Anesthetic | Ketamine |  | Propofol
Preanesthetic | Saline n=37 | Dexmedetomidine n=64 | Saline n=31 | Dexmedetomidine n=52
Emesis | 2 | 20 | 1 | 12
Pale mucous membranes |  | 11 |  | 9
Decreased body temperature |  | 4
Retching |  | 1 | 1 | 3
Heart murmur |  |  |  | 2
Loose stool |  | 2
Corneal injury | 1
Apnea |  | 1
Behavioral change |  |  | 1
Fluid in endotracheal tube |  |  | 1

One case of apnea was reported in a cat that received ketamine as the induction agent. This cat required artificial ventilation from the start of the procedure until 30 minutes into recovery when the cat began to breathe on its own. The cat recovered without further problems.

POST APPROVAL EXPERIENCE

The following adverse events were obtained from post-approval adverse drug events reported for DEXDOMITOR sterile injectable solution from 2007-2009. Not all adverse reactions are reported. Some adverse reactions occurred when DEXDOMITOR was used alone for sedation; most occurred when DEXDOMITOR was used in the presence of anesthetics and/or other preanesthetics. It is not always possible to reliably estimate the frequency of an adverse event or to establish a causal relationship to the drug, especially when multiple drugs are administered. The following reported adverse events are listed in decreasing order of frequency:

Dogs: ineffective for sedation, death, bradycardia, cardiac arrest, apnea, convulsions, vomiting, prolonged sedation, elevated temperature, and delayed sedation.

Cats: ineffective for sedation, death, cardiac arrest, vomiting, apnea, prolonged sedation, hypersalivation, hypothermia, bradycardia, cyanotic mucous membranes, sedation too brief, and dyspnea.

INFORMATION FOR OWNERS

Owners should notify their veterinarian immediately if their cat experiences difficulty breathing due to the rare possibility of delayed onset of pulmonary edema which has been associated with administration of alpha2-adrenergic agonists in cats.

CLINICAL PHARMACOLOGY

Dexmedetomidine is a potent non-narcotic alpha2-adrenoceptor agonist which produces sedation and analgesia. These effects are dose dependent in depth and duration. Blood pressure is initially increased due to peripheral vasoconstriction, subsequently dropping to normal or slightly below normal levels. Vasoconstriction may cause mucous membranes to appear pale or mildly cyanotic. This initial vasopressor response is accompanied by a compensatory marked decrease in heart rate mediated by a vagal baroreceptor. The peripheral pulse may feel weak and a transient change in the conductivity of the cardiac muscle may occur, as evidenced by first and second degree atrioventricular blocks. Other arrhythmias may occur. Dexmedetomidine also decreases the respiratory rate and decreases body temperature. The magnitude and duration of the decrease in body temperature is dose dependent. Dexmedetomidine causes depression of gastrointestinal motility due to decrease in smooth muscle activity, increases in blood glucose levels due to inhibition of insulin release, and increases in production of urine. Spontaneous muscle contractions (twitching) can be expected in some dogs sedated with dexmedetomidine. Vomiting in cats has been associated with alpha2-adrenergic agonist central stimulation of the brain^4.

EFFECTIVENESS

Canine sedation/analgesia field study

Dexmedetomidine was evaluated in a masked, controlled, multi-site field study, using parallel treatment groups. Effectiveness was evaluated in 200 (of 213) healthy client-owned dogs, ranging in age between 16 weeks and 16 years of age, and in size between 4.8 lbs and 141 lbs (2.2 kg and 64 kg). Dogs admitted to veterinary clinics for various procedures requiring sedation and/or analgesia received either dexmedetomidine or medetomidine once, by IV or IM injection. Procedures included dental care, radiography, minor skin tumor removal, and treatment of otitis.

Sedation and analgesia occurred within 5 minutes after IV dexmedetomidine, and within 15 minutes after IM dexmedetomidine, with peak effects approximately at 15 or 30 minutes, respectively. Effects waned by approximately two hours after IV administration, and by three hours using the IM route. Dexmedetomidine and medetomidine showed comparable clinical effects.

Cardiac rhythms were evaluated by auscultation. Bradycardia occurred within 5 to 15 minutes after IV dexmedetomidine or medetomidine, and within 15 to 30 minutes after either drug given IM. Sixty-four dexmedetomidine-treated dogs and 50 medetomidine-treated dogs were observed with bradycardia.

Adverse reactions during the field study included ausculted unidentified arrhythmias, apnea, hypothermia, and ineffectiveness (see ADVERSE REACTIONS).

Eleven dogs received concomitant medication during the field study, including amoxicillin, cephalexin, triamcinolone, methyl-prednisolone acetate, neomycin, nystatin, thiostrepton, acepromazine, atropine, and atipamezole.

The results of this field study demonstrate that dexmedetomidine produces satisfactory levels of sedation and analgesia for clinical examinations and procedures, minor surgical procedures, and minor dental procedures.

Canine preanesthesia field study

The use of dexmedetomidine as a preanesthetic was evaluated in a controlled, multi-site field study, using parallel treatment groups. Effectiveness was evaluated in 192 healthy, client-owned dogs, between 5 months and 15 years of age, weighing 4 to 196 lbs (2 kg to 89 kg). Dogs received IM dexmedetomidine or saline as a preanesthetic to general anesthesia. All dogs were induced by an injectable anesthetic; half of the dogs were maintained with an inhalation anesthetic. Procedures included orchiectomy, ovariohysterectomy, skin surgery, radiography, physical examination, dental procedures, ear cleaning, anal sac treatment, and grooming.

Compared to saline controls, dexmedetomidine IM reduced induction drug requirements by 30-36% (at 125 mcg/m^2) and by 38-61% (at 375 mcg/m^2). Inhalation anesthetic requirements were 40-60% less for dexmedetomidine-preanesthetized dogs. The number of dogs with clinical signs of pain was less for at least 30 minutes after the procedure in dogs treated with 375 mcg/m^2 dexmedetomidine, compared to saline controls.

Recovery times were dose dependent, averaging 15-32 minutes to extubation and 71-131 minutes to standing recovery (longer times correspond to higher dexmedetomidine dose). Recovery times also depended on the induction anesthetic. Recovery times following barbiturate induction were longer (30 minutes to extubation and 118 minutes to standing), compared to dogs induced with propofol (23 minutes to extubation and 84 minutes to standing).

Cardiac arrhythmias were monitored by ECG. Dexmedetomidine-treated dogs were more frequently observed with at least one incidence of arrhythmia compared to saline controls. The most commonly observed arrhythmias were bradycardia, 1st and 2nd degree AV block, and sinus arrest. Other less frequently observed arrhythmias included ventricular premature complexes (VPCs), supraventricular premature complexes, 3rd degree AV block, and sinus pause.

Adverse events included bradycardia, tachycardia, VPCs, vomiting, diarrhea, urinary incontinence, and self trauma (see ADVERSE REACTIONS).

The results of the preanesthesia field study demonstrate that dexmedetomidine provided anesthetic dose-sparing, sedation, and analgesia during procedures conducted under general anesthesia.

Feline sedation/analgesia field study

DEXDOMITOR was evaluated in a masked, controlled, multiple site field study, using parallel treatment groups. Effectiveness was evaluated in 242 client-owned cats, ranging in age between 6 months and 17 years, and in size between 2.3 and 9.6 kg (5 and 21 lbs). Cats admitted to veterinary clinics for various procedures requiring restraint, sedation, and/or analgesia were randomized to treatment group and given dexmedetomidine (122 cats) or xylazine (120 cats) once by IM injection. Procedures performed using dexmedetomidine included dental care, radiography, minor superficial surgery, otitis treatment, blood or urine sample collection, tattooing, microchip placement, and grooming.

Sedation and analgesia occurred within 5 to 15 minutes and peak effects were observed 30 minutes after dexmedetomidine. The procedure was easily performed in 91% of cats beginning 30 minutes after dexmedetomidine. Sedative and analgesic effects waned by three hours after dexmedetomidine.

Signs of sedation were deeper for cats receiving dexmedetomidine compared to those receiving xylazine. No clinically relevant differences were observed between dexmedetomidine and xylazine with respect to analgesia or physiological variables. Heart rate, respiratory rate, and rectal temperature decreased. Bradycardia was observed within 5 to 15 minutes and heart rates of ≤70 beats/minute were seen in 18% of cats. The most commonly observed arrhythmias assessed with ECG were atrioventricular dissociation and escape rhythms, followed by a few incidences of premature complexes and one incidence of atrioventricular block. Oxygen saturation, mucous membrane color, capillary refill time, pulse character, respiratory depth and pattern, and response of the animal to injection were clinically satisfactory. All cats recovered from changes induced by dexmedetomidine.

Ninety-seven adverse events were reported after dexmedetomidine. The most frequently reported adverse reactions included vomiting (70), urinary incontinence (6), hypersalivation (4), involuntary defecation (4), hypothermia (2), and diarrhea (2) (see ADVERSE REACTIONS).

The results of this field study demonstrate that dexmedetomidine produces satisfactory levels of sedation and analgesia for clinical examinations and procedures, minor surgical procedures, and minor dental procedures.

Feline preanesthesia field study

The use of dexmedetomidine as a preanesthetic was evaluated in a masked, controlled, multi-site field study, using parallel treatment groups. Effectiveness was evaluated in 182 healthy, client-owned cats, between 12 weeks and 16 years of age, weighing 2.10 to 18.8 lbs (0.9 kg to 8.5 kg). Preanesthetic/induction drug regimens included saline/ketamine, dexmedetomidine/ketamine, saline/propofol, and dexmedetomidine/propofol. All cats were intubated prior to the procedure. Inhalant anesthesia (isoflurane) was added during longer procedures (>15 minutes) and could be added during shorter procedures if the veterinarian deemed it necessary. Procedures included ovariohysterectomy, orchiectomy, onychectomy, and dental cleaning.

Dexmedetomidine IM administered at 40 mcg/kg prior to induction with ketamine resulted in a significantly higher proportion of cats that were successfully intubated compared to saline (success rates of 89.5% and 10.7%, respectively).

Cats preanesthetized with dexmedetomidine IM required 48.9% less propofol for successful intubation compared to cats that received saline. Inhalant anesthetic requirements were 35-44% less for dexmedetomidine preanesthetized cats. Recovery times following ketamine and propofol induction averaged 36 and 38 minutes to extubation and 161 and 131 minutes to standing, respectively for dexmedetomidine-treated groups.

Dexmedetomidine (followed by ketamine or propofol) resulted in the following ECG abnormalities (in decreasing order of frequency): sinus bradycardia, sinus arrhythmia, 1st degree atrioventricular (AV) block, long QT interval, sinus pauses, ventricular premature depolarizations, 2nd degree AV block, escape beats/rhythms, and supraventricular premature depolarizations. Dexmedetomidine-treated cats had a lower mean heart rate, respiratory rate, and body temperature compared to saline controls continuing through the recovery period.

Sixty-six adverse events were reported after dexmedetomidine. The most frequently reported adverse events were: vomiting (32), pale mucous membranes (20), decreased body temperature (4), and retching (4). (See ADVERSE REACTIONS).

ANIMAL SAFETY

Canine safety study

In the multiple dose safety study, dexmedetomidine was administered at 0, 1, 3 or 5 times (X) the recommended IV and IM doses on 3 consecutive days to a total of 36 healthy, young beagles. Two additional groups were given a 3X dose of dexmedetomidine (IV or IM) followed by three 1X doses of the reversal agent, atipamezole (ANTISEDAN), every 30 minutes. This was repeated for a total of 3 days. No deaths occurred during the study.
1X dose group: At the recommended dose, sedation lasted less than 3 hours. During sedation, muscle twitches occurred intermittently, and decreases in temperature, respiratory rate and heart rate were observed in all animals. A slow pupil response to light was seen transiently about 15 minutes after dosing in one of twelve dogs. Second degree atrioventricular (AV) blocks were observed in one of twelve dogs.
3X dose group: At 3 times the recommended dose, the duration of sedation was between two and eight hours. During sedation, muscle twitches occurred, and temperature, respiratory rate, and heart rate decreased in all dogs. The pupillary light reflex was transiently decreased for up to 90 minutes in four of twelve dogs. Vomiting was seen in two of twelve dogs. One dog experienced first and second degree AV blocks; second degree AV block was observed in three of twelve dogs. Elevated concentrations of alanine aminotransferase (ALT) were observed in one dog, without histological changes to the liver.
5X dose group: At 5 times the recommended dose, the duration of sedation was between four and eight hours. Muscle twitches, decreases in temperature, respiratory rates, and heart rates were seen in all dogs. No pupil response was noted in six of twelve dogs (IV) for up to 1.5 hours; decreased transient pupillary light reflex was seen for up to 60 minutes in two of twelve dogs (IM). Vomiting was seen in one of twelve dogs. First and second degree AV blocks were observed in one of twelve dogs. Elevated concentrations of ALT were observed in 3 of 12 dogs, without histological changes to the liver.
Dexmedetomidine demonstrated dose dependent effects related to its pharmacology when administered IV or IM to healthy dogs at doses up to five times the recommended dose.

Canine safety study with an anticholinergic

In another laboratory safety study, one of three doses of an IM anticholinergic drug or saline was administered 10 minutes before, at the same time, or 15 minutes after 500 mcg/m^2 IM dexmedetomidine. The anticholinergic drug was given for the prevention or treatment of dexmedetomidine-induced reduction in heart rate. In a crossover design, 18 dogs were used in a total of 72 trials, to evaluate the safety of dexmedetomidine used with an anticholinergic drug.

Dogs were instrumented for the accumulation of continuous ECG data. The following arrhythmias were recorded during the study (some dogs experienced more than one arrhythmia).

Table 8: Arrhythmias recorded during the canine laboratory safety study [Table does not relate arrhythmias to the presence or absence of anticholinergic]
Type of arrhythmia | Number of dogs (of 18)
Second degree AV block | 18
Supraventricular tachycardia (SVT) or SVPCs | 16
Ventricular escape beats | 16
Ventricular premature contractions | 14
Third degree AV block | 6
Idioventricular rhythm | 1
Paroxysmal VT | 1
Ventricular bigeminy; SVPCs; pulse alternans | 1
Junctional escape beat | 1

The occurrence of arrhythmias was not related to the presence or absence of the anticholinergic drug. Arrhythmias were transient (although frequent over time in some dogs), returning toward baseline levels within 55 minutes after dexmedetomidine. No dogs required treatment related to these arrhythmias, and none of these arrhythmias persisted or adversely affected the overall clinical status of any dog in the study.

Dexmedetomidine without anticholinergic: Without the anticholinergic drug, and in addition to arrhythmias, dexmedetomidine produced clinically relevant sedation accompanied by a statistically significant reduction in heart rate, respiratory rate, cardiac output, pulmonary arterial temperature, and mixed venous oxygen tension. A statistically significant increase in arterial blood pressure, pulmonary capillary wedge pressure, central venous pressure, and systemic vascular resistance was noted. No dogs experienced hypotension. Dexmedetomidine tended to increase pulmonary vascular resistance. Dexmedetomidine alone had no statistically significant effect on mean pulmonary arterial pressure, arterial pH, arterial carbon dioxide tension, and arterial oxygen tension.
Dexmedetomidine plus anticholinergic: Either of the two higher anticholinergic doses was effective in the prevention or treatment of the dexmedetomidine-induced reduction in heart rate. Anticholinergic (higher doses) given after dexmedetomidine caused marked increases in the occurrence of various cardiac arrhythmias, especially second degree AV block. When the higher doses of anticholinergic drug were given at the same time or 15 minutes after dexmedetomidine, large increases in heart rate (p<0.01) and blood pressure (p<0.05) were seen. Increases were dose related; the highest anticholinergic dose elicited more frequent arrhythmias and larger increases in heart rate and blood pressure.
In conclusion, moderate doses of anticholinergic drug given prior to dexmedetomidine performed best for the prevention of dexmedetomidine-induced reduction of heart rate in dogs. The routine use of anticholinergics given simultaneously with, or after dexmedetomidine, is not recommended.

Feline safety study

In a multiple dose safety study, DEXDOMITOR was administered intramuscularly (IM) at 1×, 3×, and 5× (40, 120, and 200 mcg/kg) the recommended dose of 40 mcg/kg on 3 consecutive days to healthy cats, 6 to 8 months old. A control group received the product vehicle as a placebo (0×). No mortality was observed. The depth and duration of sedation was dose dependent, lasting approximately 2 hours in the 1× group, 2 to 4 hours in the 3× group, and greater than 8 hours in the 5× group. The lowest recorded individual heart rate was 60 beats/minute and occurred in the 5× dose group (2 cats). Cardiac arrhythmias characterized by isolated junctional escape complexes with episodes of junctional escape rhythm were observed during periods of low heart rate or following sinus pauses in all dexmedetomidine dose groups. In most cases the arrhythmia was no longer observed after 1 to 2 hours. Atrioventricular block was not observed. Incidences of arrhythmias were not related to dose; however, more cats were affected by cardiac arrhythmias on the third day of treatment, compared to the first two days of the study. The decrease in respiratory rate, but not the duration, was dose dependent. The rectal temperature decreased in all dexmedetomidine-treated groups, with the lowest temperatures in the 5× group at 8 hours on all three days. Two cats vomited (40 and 120 mcg/kg). Corneal opacity was noted in all dexmedetomidine-dose groups, was transient, related to dose and duration of sedation, and was attributed to lack of lubrication with decreased blinking during sedation. Hematology and blood chemistry were unaffected by treatment. Injection site tolerance was good, with mild inflammatory lesions representative of the IM injection procedure. Gross and histological examination of all other tissues did not reveal any abnormalities related to DEXDOMITOR administration.

Dexmedetomidine demonstrated dose dependent effects related to its pharmacology when administered IM to healthy cats at doses up to five times the recommended dose.

Feline acute tolerance study

IM DEXDOMITOR was administered once at 10X (400 mcg/kg) the recommended dose of 40 mcg/kg to 3 female and 3 male 7 month old cats. No mortality was observed. Sedation was observed within 15 minutes of dosing and lasted for at least 4 hours with full recovery noted between 8 and 24 hours after dosing. Transient observations of corneal dehydration and opacity, miosis, pale skin and gingiva, salivation, and watery ocular discharge were observed in some animals. Vomiting was observed 7 to 11 hours after dosing in all but one animal. Decreases in heart rate accompanied by prolonged PQ and QT intervals were most pronounced 2 to 4 hours after dosing. No atrioventricular (AV) blocks or escape rhythms were noted. In one cat, incidental and reversible premature junctional complexes were seen at 1 and 2 hours after dosing which were considered secondary to bradycardia. Slightly lower respiratory rate and reduced rectal temperature were observed 4 to 8 hours after dosing. Observations had returned to normal by 24 hours after dosing. Mild inflammatory lesions observed histologically at the injection site were representative of the IM injection procedure. No treatment related changes were observed in hematology. Mild elevations in some clinical ALT, AST, and CK, were observed 24 hours after dosing, with a trend towards recovery by 48 hours. Total protein, albumin and globulin levels were slightly lowered in one cat 48 hours after dosing.

STORAGE INFORMATION

Store at controlled room temperature 15-30°C (59-86°F). Protect from freezing. In use shelf life: 90 days at 25°C (77°F).

HOW SUPPLIED

DEXDOMITOR 0.1 mg/mL is supplied in 20-mL multidose vials with filling volume of 15 mL containing 0.1 mg of dexmedetomidine hydrochloride per mL.

REFERENCES

(1) Ko JCH, Fox SMF, Mandsager RE. Effects of preemptive atropine administration on incidence of medetomidine-induced bradycardia in dogs. J Am Vet Med Assoc 2001; 218:52-58.
(2) Alibhai HIK, Clarke KW, Lee YH, et al. Cardiopulmonary effects of combinations of medetomidine hydrochloride and atropine sulphate in dogs. Vet Rec 1996; 138:11-13.
(3) Short, CE. Effects of anticholinergic treatment on the cardiac and respiratory systems in dogs sedated with medetomidine. Vet Rec 1991; 129:310-313.
(4) Hikasa Y, Akiba T, Iino Y et al. Cen tral alpha-adrenoceptor subtypes involved in the emetic pathway in cats. Eur J Pharmacol 1992; 229:241-251.

U.S. Patent No. 4,910,214
DEXDOMITOR® is a trademark of Orion Corporation.

Approved by FDA under NADA # 141-267

Mfd by:
Orion Pharma
Orion Corporation
Espoo, Finland
Dist by:
zoetis
Zoetis Inc.
Kalamazoo, MI 49007
Revised: December 2022
144440-3
122691-7

DEXDOMITOR®
(dexmedetomidine hydrochloride)
Sterile Injectable Solution – 0.5 mg/mL
Intramuscular and Intravenous use in Dogs
Intramuscular use in Cats
Sedative, Analgesic, Preanesthetic

CAUTION

Federal law restricts this drug to use by or on the order of a licensed veterinarian.

DESCRIPTION

DEXDOMITOR (dexmedetomidine hydrochloride) is a synthetic alpha2-adrenoreceptor agonist with sedative and analgesic properties. The chemical name is (+)-4-[1-(2,3-dimethylphenyl) ethyl]-1H-imidazole monohydrochloride. It is a white, or almost white, crystalline, water soluble substance having a molecular weight of 236.7. The molecular formula is C13 H16 N2 ∙HCl and the structural formula is:

0.5 - Each mL of DEXDOMITOR contains 0.5 mg dexmedetomidine hydrochloride, 1.6 mg methylparaben (NF), 0.2 mg propylparaben (NF), 9.0 mg sodium chloride (USP), and water for injection (USP), q.s.

INDICATIONS

DEXDOMITOR is indicated for use as a sedative and analgesic in dogs and cats to facilitate clinical examinations, clinical procedures, minor surgical procedures, and minor dental procedures. DEXDOMITOR is also indicated for use as a preanesthetic to general anesthesia in dogs and cats.

DOSAGE AND ADMINISTRATION

Dogs - 0.5

Sedation and Analgesia: 500 mcg/m^2 intramuscularly (IM) or 375 mcg/m^2 intravenously (IV). Preanesthesia: 125 or 375 mcg/m^2 IM.

The choice of preanesthetic dose depends on the duration and severity of the procedure, as well as the anesthetic regime. The following two tables may be used to determine the correct dexmedetomidine dosage. Note that the mcg/kg dosage decreases as body weight increases. For example, dogs weighing 2 kg are dosed at 28.1 mcg/kg dexmedetomidine IV, compared to dogs weighing 80 kg that are dosed at 8.7 mcg/kg. Due to the small volume of administration, accurate dosing is not possible in dogs weighing less than 2 kg (4.4 lb).

Table 1: CANINE SEDATION/ANALGESIA DOSE TABLE: Intravenous (IV) and intramuscular (IM) dosing on the basis of body weight.
DEXDOMITOR 0.5 mg/mL
Sedation/analgesia in dogs
Dog Weight |  | Dexmedetomidine 375 mcg/m^2 IV |  | Dexmedetomidine 500 mcg/m^2 IM
lbs | Kg | mcg/kg | mL | mcg/kg | mL
4.4-7 | 2-3 | 28.1 | 0.12 | 40 | 0.15
7.1-9 | 3.1-4 | 25 | 0.15 | 35 | 0.2
9.1-11 | 4.1-5 | 23 | 0.2 | 30 | 0.3
11.1-22 | 5.1-10 | 19.6 | 0.29 | 25 | 0.4
22.1-29 | 10.1-13 | 16.8 | 0.38 | 23 | 0.5
29.1-33 | 13.1-15 | 15.7 | 0.44 | 21 | 0.6
33.1-44 | 15.1-20 | 14.6 | 0.51 | 20 | 0.7
44.1-55 | 20.1-25 | 13.4 | 0.6 | 18 | 0.8
55.1-66 | 25.1-30 | 12.6 | 0.69 | 17 | 0.9
66.1-73 | 30.1-33 | 12 | 0.75 | 16 | 1
73.1-81 | 33.1-37 | 11.6 | 0.81 | 15 | 1.1
81.1-99 | 37.1-45 | 11 | 0.9 | 14.5 | 1.2
99.1-110 | 45.1-50 | 10.5 | 0.99 | 14 | 1.3
110.1-121 | 50.1-55 | 10.1 | 1.06 | 13.5 | 1.4
121.1-132 | 55.1-60 | 9.8 | 1.13 | 13 | 1.5
132.1-143 | 60.1-65 | 9.5 | 1.19 | 12.8 | 1.6
143.1-154 | 65.1-70 | 9.3 | 1.26 | 12.5 | 1.7
154.1-176 | 70.1-80 | 9 | 1.35 | 12.3 | 1.8
>176 | >80 | 8.7 | 1.42 | 12 | 1.9

Table 2: CANINE PREANESTHESIA DOSE TABLE: Intramuscular (IM) dosing on the basis of body weight.
DEXDOMITOR 0.5 mg/mL
Preanesthesia in dogs
Dog Weight |  | Dexmedetomidine 125 mcg/m^2 IM |  | Dexmedetomidine 375 mcg/m^2 IM
lbs | Kg | mcg/kg | mL | mcg/kg | mL
4.4-7 | 2-3 | 9.4 | 0.04 | 28.1 | 0.12
7.1-9 | 3.1-4 | 8.3 | 0.05 | 25 | 0.15
9.1-11 | 4.1-5 | 7.7 | 0.07 | 23 | 0.2
11.1-22 | 5.1-10 | 6.5 | 0.1 | 19.6 | 0.29
22.1-29 | 10.1-13 | 5.6 | 0.13 | 16.8 | 0.38
29.1-33 | 13.1-15 | 5.2 | 0.15 | 15.7 | 0.44
33.1-44 | 15.1-20 | 4.9 | 0.17 | 14.6 | 0.51
44.1-55 | 20.1-25 | 4.5 | 0.2 | 13.4 | 0.6
55.1-66 | 25.1-30 | 4.2 | 0.23 | 12.6 | 0.69
66.1-73 | 30.1-33 | 4 | 0.25 | 12 | 0.75
73.1-81 | 33.1-37 | 3.9 | 0.27 | 11.6 | 0.81
81.1-99 | 37.1-45 | 3.7 | 0.3 | 11 | 0.9
99.1-110 | 45.1-50 | 3.5 | 0.33 | 10.5 | 0.99
110.1-121 | 50.1-55 | 3.4 | 0.35 | 10.1 | 1.06
121.1-132 | 55.1-60 | 3.3 | 0.38 | 9.8 | 1.13
132.1-143 | 60.1-65 | 3.2 | 0.4 | 9.5 | 1.19
143.1-154 | 65.1-70 | 3.1 | 0.42 | 9.3 | 1.26
154.1-176 | 70.1-80 | 3 | 0.45 | 9 | 1.35
>176 | >80 | 2.9 | 0.47 | 8.7 | 1.42

The use of dexmedetomidine as a preanesthetic markedly reduces anesthetic requirements in dogs. Injectable induction drug requirements for intubation will be reduced between 30% and 60%, depending on the choice of anesthetic and the dexmedetomidine preanesthetic dose. The concentration of inhalation maintenance anesthetic will be reduced between 40% and 60%, depending on the dose of dexmedetomidine. The anesthetic dose should always be titrated against the response of the patient. The choice of anesthetic is left to the discretion of the veterinarian.

Cats - 0.5

Sedation, Analgesia and Preanesthesia: 40 mcg/kg intramuscularly (IM).

This dose can also be used as a preanesthetic and has been shown to markedly reduce anesthetic requirements in cats. Injectable anesthetic drug requirements for intubation were reduced up to 49%, depending on the choice of induction drug. The concentration of inhalation maintenance anesthetic was reduced between 35% and 44%, depending on the choice of induction drug. The anesthetic dose should always be titrated against the response of the patient.

The following table may be used to determine the correct dexmedetomidine dosage for cats based on body weight.

Table 3: FELINE DOSE TABLE: Intramuscular (IM) dosing on the basis of body weight in cats.
DEXDOMITOR 0.5 mg/mL
Sedation/analgesia and preanesthesia in cats
Cat Weight |  | Dexmedetomidine 40 mcg/kg IM
lbs | kg | mcg/kg | mL
2-4 | 1-2 | 40 | 0.1
4.1-7 | 2.1-3 | 40 | 0.2
7.1-9 | 3.1-4 | 40 | 0.3
9.1-13 | 4.1-6 | 40 | 0.4
13.1-15 | 6.1-7 | 40 | 0.5
15.1-18 | 7.1-8 | 40 | 0.6
18.1-22 | 8.1-10 | 40 | 0.7

It is recommended that dogs and cats be fasted for 12 hours before treatment with DEXDOMITOR. An eye lubricant should be applied to cats to prevent corneal desiccation that may result from a reduction in the blink reflex. Following injection of DEXDOMITOR, the animal should be allowed to rest quietly for 15 minutes; sedation and analgesia occur within 5 to 15 minutes, with peak effects at 30 minutes after dexmedetomidine.

CONTRAINDICATIONS

Do not use DEXDOMITOR in dogs or cats with cardiovascular disease, respiratory disorders, liver or kidney diseases, or in conditions of shock, severe debilitation, or stress due to extreme heat, cold or fatigue.

As with all alpha2-adrenoceptor agonists, the potential for isolated cases of hypersensitivity, including paradoxical response (excitation), exists.

WARNINGS

Human safety: Not for human use. Keep out of reach of children.
Dexmedetomidine hydrochloride can be absorbed following direct exposure to skin, eyes, or mouth, and may cause irritation. In case of accidental eye exposure, flush with water for 15 minutes. In case of accidental skin exposure, wash with soap and water. Remove contaminated clothing.
Appropriate precautions should be taken while handling and using filled syringes. Accidental topical (including ocular) exposure, oral exposure, or exposure by injection could cause adverse reactions, including sedation, hypotension, and bradycardia. Seek medical attention immediately.
Users with cardiovascular disease (for example, hypertension or ischemic heart disease) should take special precautions to avoid any exposure to this product.
Caution should be exercised when handling sedated animals. Handling or any other sudden stimuli, including noise, may cause a defense reaction in an animal that appears to be heavily sedated.
Note to physician: This product contains an alpha2-adrenergic agonist.
Animal safety: Dexmedetomidine should not be administered in the presence of preexisting hypotension, hypoxia, or bradycardia. Due to the pronounced cardiovascular effects of dexmedetomidine, only clinically healthy dogs and cats (ASA classes I and II) should be treated. Animals should be frequently monitored for cardiovascular function and body temperature during sedation or anesthesia. Dexmedetomidine sedation is not recommended for cats with respiratory disease.
The use of dexmedetomidine as a preanesthetic in dogs and cats significantly reduces the amount of induction and maintenance anesthetic requirements. Careful patient monitoring during anesthetic induction and maintenance is necessary to avoid anesthetic overdose.

CONTACT INFORMATION

For a copy of the Safety Data Sheet or to report adverse reactions, call Zoetis Inc. at 1-888-963-8471. For additional information about adverse drug experience reporting for animal drugs, contact FDA at 1-888-FDA-VETS or www.fda.gov/reportanimalae.

PRECAUTIONS

Apnea may occur with dexmedetomidine use. In the event of apnea, additional oxygen should be supplied. Administration of ANTISEDAN (atipamezole) to dogs is warranted when apnea is accompanied by bradycardia and cyanotic mucous membranes.
Adverse reaction reports for dexmedetomidine in cats include rare events of severe dyspnea and respiratory crackles diagnosed as acute pulmonary edema. Dyspnea due to the delayed onset of pulmonary edema could develop in rare instances up to three days after dexmedetomidine administration. Some of these acute and delayed pulmonary edema cases have resulted in death although this was not observed in the feline clinical field studies with dexmedetomidine.
In dogs, intramuscular ANTISEDAN (atipamezole) may be routinely used to rapidly reverse the effects of dexmedetomidine. Since analgesic as well as sedative effects will be reversed, pain management may need to be addressed.
In cats, ANTISEDAN (atipamezole) has not been evaluated as a routine dexmedetomidine reversal agent. In cats, cases of dyspnea following ANTISEDAN (atipamezole) administration have been reported.
Dexmedetomidine has not been evaluated in the presence of other preanesthetics in cats. Although not observed in the feline field studies, death has been reported in cats receiving dexmedetomidine in conjunction with ketamine and butorphanol.
Analgesia resulting from preanesthetic dexmedetomidine may not provide adequate pain control during the postoperative or postprocedural period. Additional pain management should be addressed as needed.
Following administration of dexmedetomidine, a decrease in body temperature is likely to occur unless externally maintained. Once established, hypothermia may persist longer than sedation and analgesia. To prevent hypothermia, treated animals should be kept warm and at a constant temperature during the procedure, and until full recovery.
Nervous or excited animals with high levels of endogenous catecholamines may exhibit a reduced pharmacological response to alpha2-adrenoceptor agonists like dexmedetomidine (ineffectiveness). In agitated animals, the onset of sedative/analgesic effects could be slowed, or the depth and duration of effects could be diminished or nonexistent. Therefore, allow dogs and cats to rest quietly for 10 to 15 minutes after injection. Repeat dosing has not been evaluated.
Administration of anticholinergic agents in dogs or cats at the same time or after dexmedetomidine could lead to adverse cardiovascular effects (secondary tachycardia, prolonged hypertension, and cardiac arrhythmias1, 2, 3). However, an anticholinergic drug may be administered to dogs at least 10 minutes before dexmedetomidine for the prevention of the dexmedetomidine-induced reduction in heart rate. Therefore, the routine use of anticholinergics simultaneously with, or after dexmedetomidine in dogs or cats, is not recommended (see ANIMAL SAFETY).
Spontaneous muscle contractions (twitching) can be expected in some dogs sedated with dexmedetomidine.
Dexmedetomidine has been evaluated only in fasted dogs; therefore, its effects on fed dogs (for example, the occurrence of vomiting) have not been characterized. In cats, there is a high frequency of vomition whether fed or fasted; therefore, fasting is recommended to reduce stomach contents.
Dexmedetomidine has not been evaluated in dogs younger than 16 weeks of age, in cats younger than 12 weeks of age, or in geriatric dogs and cats.
Dexmedetomidine has not been evaluated for use in breeding, pregnant, or lactating dogs or cats.

ADVERSE REACTIONS

Canine sedation/analgesia field study

In the field study safety analysis, 106 dogs received dexmedetomidine and 107 received medetomidine. Dogs ranged from 16 weeks to 16 years of age, representing 49 breeds. The following table shows the number of dogs displaying each clinical observation (some dogs experienced more than one adverse reaction).

Table 4: Adverse reactions during the canine sedation/analgesia field study
 | Dexmedetomidine Total n= 106 | Medetomidine Total n=107
Ausculted unidentified arrhythmias | 19 | 20
Severe bradycardia requiring treatment | 1 | 1
Apnea requiring treatment | 1 | 0
Slow onset of sedation (exceeding 30 minutes) | 1 | 1
Ineffectiveness (dog standing throughout the study) | 3 | 2
Severe hypothermia requiring treatment | 2 | 0
Prolonged recovery | 1 | 4

The occurrence of ausculted unidentified arrhythmias (some at multiple time points) decreased following the administration of atipamezole.

Canine preanesthesia field study

The preanesthesia field study safety analysis included 192 dogs, between 5 months and 15 years of age, representing 43 breeds enrolled for elective procedures conducted under general anesthesia. The following table shows the number of dogs within a treatment group that showed each clinical sign (dogs may have experienced more than one adverse reaction).

Table 5: Adverse reactions during the canine preanesthesia field study
 | Treatment Groups
Induction Anesthetic: | Propofol |  |  | Barbiturate
Preanesthetic Dose: | 0 mcg/m^2 n=32 | 125 mcg/m^2 n=32 | 375 mcg/m^2 n=32 | 0 mcg/m^2 n=32 | 125 mcg/m^2 n=32 | 375 mcg/m^2 n=32
Emesis | 4 | 7 | 4 | 2 | 3 | 6
Ventricular premature contractions | 0 | 2 | 0 | 4 | 1 | 0
Diarrhea | 1 | 0 | 0 | 3 | 1 | 1
Self trauma | 0 | 2 | 1 | 2 | 1 | 0
Severe bradycardia | 0 | 0 | 1 | 0 | 0 | 1
Tachycardia | 0 | 0 | 0 | 1 | 1 | 0
Urinary incontinence | 0 | 0 | 0 | 0 | 0 | 1

Other clinical signs observed in dogs treated with dexmedetomidine include decreased respiratory rate and hypothermia.

Feline sedation/analgesia field study

The field study safety analysis included 242 cats (122 received dexmedetomidine; 120 received xylazine), 6 months to 17 years of age, and representing 19 breeds. The following table shows the number of cats reported with an adverse reaction (cats may have experienced more than one adverse reaction).

Table 6: Adverse reactions during the feline field study
 | Dexmedetomidine n = 122 | Xylazine n = 120
Vomiting | 70 | 82
Urinary incontinence | 6 | 11
Hypersalivation | 4 | 5
Involuntary defecation | 4 | 1
Hypothermia | 2 | 1
Diarrhea | 2 | 0
Arrhythmia | 1 | 2
Corneal ulcer | 1 | 0
Cyanosis | 1 | 0
Dyspnea | 1 | 0

The most frequently observed adverse reaction was vomiting in both fasted and fed cats. Other infrequent clinical signs observed in cats treated with dexmedetomidine included fatigue, anorexia, cystitis, and peripheral vascular disorder.

One incidence of dyspnea was reported, 43 minutes after dexmedetomidine administration during an oral examination/dental procedure. Prior to dexmedetomidine, the cat was free of clinical signs, but had a history of asthma and respiratory infection. The cat responded successfully to treatment.

Feline preanesthesia field study

The field study safety analysis included 184 cats (116 received dexmedetomidine; 68 received saline), 12 weeks to 16 years of age, and representing 11 breeds. The following table shows the number of cats reported with an adverse reaction (cats may have experienced more than one adverse reaction).

Table 7. Adverse reactions during the feline preanesthesia field study
Induction Anesthetic | Ketamine |  | Propofol
Preanesthetic | Saline n=37 | Dexmedetomidine n=64 | Saline n=31 | Dexmedetomidine n=52
Emesis | 2 | 20 | 1 | 12
Pale mucous membranes |  | 11 |  | 9
Decreased body temperature |  | 4
Retching |  | 1 | 1 | 3
Heart murmur |  |  |  | 2
Loose stool |  | 2
Corneal injury | 1
Apnea |  | 1
Behavioral change |  |  | 1
Fluid in endotracheal tube |  |  | 1

One case of apnea was reported in a cat that received ketamine as the induction agent. This cat required artificial ventilation from the start of the procedure until 30 minutes into recovery when the cat began to breathe on its own. The cat recovered without further problems.

POST APPROVAL EXPERIENCE

The following adverse events were obtained from post-approval adverse drug events reported for DEXDOMITOR sterile injectable solution from 2007-2009. Not all adverse reactions are reported. Some adverse reactions occurred when DEXDOMITOR was used alone for sedation; most occurred when DEXDOMITOR was used in the presence of anesthetics and/or other preanesthetics. It is not always possible to reliably estimate the frequency of an adverse event or to establish a causal relationship to the drug, especially when multiple drugs are administered. The following reported adverse events are listed in decreasing order of frequency:

Dogs: ineffective for sedation, death, bradycardia, cardiac arrest, apnea, convulsions, vomiting, prolonged sedation, elevated temperature, and delayed sedation.

Cats: ineffective for sedation, death, cardiac arrest, vomiting, apnea, prolonged sedation, hypersalivation, hypothermia, bradycardia, cyanotic mucous membranes, sedation too brief, and dyspnea.

INFORMATION FOR OWNERS

Owners should notify their veterinarian immediately if their cat experiences difficulty breathing due to the rare possibility of delayed onset of pulmonary edema which has been associated with administration of alpha2-adrenergic agonists in cats.

CLINICAL PHARMACOLOGY

Dexmedetomidine is a potent non-narcotic alpha2-adrenoceptor agonist which produces sedation and analgesia. These effects are dose dependent in depth and duration. Blood pressure is initially increased due to peripheral vasoconstriction, subsequently dropping to normal or slightly below normal levels. Vasoconstriction may cause mucous membranes to appear pale or mildly cyanotic. This initial vasopressor response is accompanied by a compensatory marked decrease in heart rate mediated by a vagal baroreceptor. The peripheral pulse may feel weak and a transient change in the conductivity of the cardiac muscle may occur, as evidenced by first and second degree atrioventricular blocks. Other arrhythmias may occur. Dexmedetomidine also decreases the respiratory rate and decreases body temperature. The magnitude and duration of the decrease in body temperature is dose dependent. Dexmedetomidine causes depression of gastrointestinal motility due to decrease in smooth muscle activity, increases in blood glucose levels due to inhibition of insulin release, and increases in production of urine. Spontaneous muscle contractions (twitching) can be expected in some dogs sedated with dexmedetomidine. Vomiting in cats has been associated with alpha2-adrenergic agonist central stimulation of the brain^4.

EFFECTIVENESS

Canine sedation/analgesia field study

Dexmedetomidine was evaluated in a masked, controlled, multi-site field study, using parallel treatment groups. Effectiveness was evaluated in 200 (of 213) healthy client-owned dogs, ranging in age between 16 weeks and 16 years of age, and in size between 4.8 lbs and 141 lbs (2.2 kg and 64 kg). Dogs admitted to veterinary clinics for various procedures requiring sedation and/or analgesia received either dexmedetomidine or medetomidine once, by IV or IM injection. Procedures included dental care, radiography, minor skin tumor removal, and treatment of otitis.

Sedation and analgesia occurred within 5 minutes after IV dexmedetomidine, and within 15 minutes after IM dexmedetomidine, with peak effects approximately at 15 or 30 minutes, respectively. Effects waned by approximately two hours after IV administration, and by three hours using the IM route. Dexmedetomidine and medetomidine showed comparable clinical effects.

Cardiac rhythms were evaluated by auscultation. Bradycardia occurred within 5 to 15 minutes after IV dexmedetomidine or medetomidine, and within 15 to 30 minutes after either drug given IM. Sixty-four dexmedetomidine-treated dogs and 50 medetomidine-treated dogs were observed with bradycardia.

Adverse reactions during the field study included ausculted unidentified arrhythmias, apnea, hypothermia, and ineffectiveness (see ADVERSE REACTIONS).

Eleven dogs received concomitant medication during the field study, including amoxicillin, cephalexin, triamcinolone, methyl-prednisolone acetate, neomycin, nystatin, thiostrepton, acepromazine, atropine, and atipamezole.

The results of this field study demonstrate that dexmedetomidine produces satisfactory levels of sedation and analgesia for clinical examinations and procedures, minor surgical procedures, and minor dental procedures.

Canine preanesthesia field study

The use of dexmedetomidine as a preanesthetic was evaluated in a controlled, multi-site field study, using parallel treatment groups. Effectiveness was evaluated in 192 healthy, client-owned dogs, between 5 months and 15 years of age, weighing 4 to 196 lbs (2 kg to 89 kg). Dogs received IM dexmedetomidine or saline as a preanesthetic to general anesthesia. All dogs were induced by an injectable anesthetic; half of the dogs were maintained with an inhalation anesthetic. Procedures included orchiectomy, ovariohysterectomy, skin surgery, radiography, physical examination, dental procedures, ear cleaning, anal sac treatment, and grooming.

Compared to saline controls, dexmedetomidine IM reduced induction drug requirements by 30-36% (at 125 mcg/m^2) and by 38-61% (at 375 mcg/m^2). Inhalation anesthetic requirements were 40-60% less for dexmedetomidine-preanesthetized dogs. The number of dogs with clinical signs of pain was less for at least 30 minutes after the procedure in dogs treated with 375 mcg/m^2 dexmedetomidine, compared to saline controls.

Recovery times were dose dependent, averaging 15-32 minutes to extubation and 71-131 minutes to standing recovery (longer times correspond to higher dexmedetomidine dose). Recovery times also depended on the induction anesthetic. Recovery times following barbiturate induction were longer (30 minutes to extubation and 118 minutes to standing), compared to dogs induced with propofol (23 minutes to extubation and 84 minutes to standing).

Cardiac arrhythmias were monitored by ECG. Dexmedetomidine-treated dogs were more frequently observed with at least one incidence of arrhythmia compared to saline controls. The most commonly observed arrhythmias were bradycardia, 1st and 2nd degree AV block, and sinus arrest. Other less frequently observed arrhythmias included ventricular premature complexes (VPCs), supraventricular premature complexes, 3rd degree AV block, and sinus pause.

Adverse events included bradycardia, tachycardia, VPCs, vomiting, diarrhea, urinary incontinence, and self trauma (see ADVERSE REACTIONS).

The results of the preanesthesia field study demonstrate that dexmedetomidine provided anesthetic dose-sparing, sedation, and analgesia during procedures conducted under general anesthesia.

Feline sedation/analgesia field study

DEXDOMITOR was evaluated in a masked, controlled, multiple site field study, using parallel treatment groups. Effectiveness was evaluated in 242 client-owned cats, ranging in age between 6 months and 17 years, and in size between 2.3 and 9.6 kg (5 and 21 lbs). Cats admitted to veterinary clinics for various procedures requiring restraint, sedation, and/or analgesia were randomized to treatment group and given dexmedetomidine (122 cats) or xylazine (120 cats) once by IM injection. Procedures performed using dexmedetomidine included dental care, radiography, minor superficial surgery, otitis treatment, blood or urine sample collection, tattooing, microchip placement, and grooming.

Sedation and analgesia occurred within 5 to 15 minutes and peak effects were observed 30 minutes after dexmedetomidine. The procedure was easily performed in 91% of cats beginning 30 minutes after dexmedetomidine. Sedative and analgesic effects waned by three hours after dexmedetomidine.

Signs of sedation were deeper for cats receiving dexmedetomidine compared to those receiving xylazine. No clinically relevant differences were observed between dexmedetomidine and xylazine with respect to analgesia or physiological variables. Heart rate, respiratory rate, and rectal temperature decreased. Bradycardia was observed within 5 to 15 minutes and heart rates of ≤70 beats/minute were seen in 18% of cats. The most commonly observed arrhythmias assessed with ECG were atrioventricular dissociation and escape rhythms, followed by a few incidences of premature complexes and one incidence of atrioventricular block. Oxygen saturation, mucous membrane color, capillary refill time, pulse character, respiratory depth and pattern, and response of the animal to injection were clinically satisfactory. All cats recovered from changes induced by dexmedetomidine.

Ninety-seven adverse events were reported after dexmedetomidine. The most frequently reported adverse reactions included vomiting (70), urinary incontinence (6), hypersalivation (4), involuntary defecation (4), hypothermia (2), and diarrhea (2) (see ADVERSE REACTIONS).

The results of this field study demonstrate that dexmedetomidine produces satisfactory levels of sedation and analgesia for clinical examinations and procedures, minor surgical procedures, and minor dental procedures.

Feline preanesthesia field study

The use of dexmedetomidine as a preanesthetic was evaluated in a masked, controlled, multi-site field study, using parallel treatment groups. Effectiveness was evaluated in 182 healthy, client-owned cats, between 12 weeks and 16 years of age, weighing 2.10 to 18.8 lbs (0.9 kg to 8.5 kg). Preanesthetic/induction drug regimens included saline/ketamine, dexmedetomidine/ketamine, saline/propofol, and dexmedetomidine/propofol. All cats were intubated prior to the procedure. Inhalant anesthesia (isoflurane) was added during longer procedures (>15 minutes) and could be added during shorter procedures if the veterinarian deemed it necessary. Procedures included ovariohysterectomy, orchiectomy, onychectomy, and dental cleaning.

Dexmedetomidine IM administered at 40 mcg/kg prior to induction with ketamine resulted in a significantly higher proportion of cats that were successfully intubated compared to saline (success rates of 89.5% and 10.7%, respectively).

Cats preanesthetized with dexmedetomidine IM required 48.9% less propofol for successful intubation compared to cats that received saline. Inhalant anesthetic requirements were 35-44% less for dexmedetomidine preanesthetized cats. Recovery times following ketamine and propofol induction averaged 36 and 38 minutes to extubation and 161 and 131 minutes to standing, respectively for dexmedetomidine-treated groups.

Dexmedetomidine (followed by ketamine or propofol) resulted in the following ECG abnormalities (in decreasing order of frequency): sinus bradycardia, sinus arrhythmia, 1st degree atrioventricular (AV) block, long QT interval, sinus pauses, ventricular premature depolarizations, 2nd degree AV block, escape beats/rhythms, and supraventricular premature depolarizations. Dexmedetomidine-treated cats had a lower mean heart rate, respiratory rate, and body temperature compared to saline controls continuing through the recovery period.

Sixty-six adverse events were reported after dexmedetomidine. The most frequently reported adverse events were: vomiting (32), pale mucous membranes (20), decreased body temperature (4), and retching (4). (See ADVERSE REACTIONS).

ANIMAL SAFETY

Canine safety study

In the multiple dose safety study, dexmedetomidine was administered at 0, 1, 3 or 5 times (X) the recommended IV and IM doses on 3 consecutive days to a total of 36 healthy, young beagles. Two additional groups were given a 3X dose of dexmedetomidine (IV or IM) followed by three 1X doses of the reversal agent, atipamezole (ANTISEDAN), every 30 minutes. This was repeated for a total of 3 days. No deaths occurred during the study.
1X dose group: At the recommended dose, sedation lasted less than 3 hours. During sedation, muscle twitches occurred intermittently, and decreases in temperature, respiratory rate and heart rate were observed in all animals. A slow pupil response to light was seen transiently about 15 minutes after dosing in one of twelve dogs. Second degree atrioventricular (AV) blocks were observed in one of twelve dogs.
3X dose group: At 3 times the recommended dose, the duration of sedation was between two and eight hours. During sedation, muscle twitches occurred, and temperature, respiratory rate, and heart rate decreased in all dogs. The pupillary light reflex was transiently decreased for up to 90 minutes in four of twelve dogs. Vomiting was seen in two of twelve dogs. One dog experienced first and second degree AV blocks; second degree AV block was observed in three of twelve dogs. Elevated concentrations of alanine aminotransferase (ALT) were observed in one dog, without histological changes to the liver.
5X dose group: At 5 times the recommended dose, the duration of sedation was between four and eight hours. Muscle twitches, decreases in temperature, respiratory rates, and heart rates were seen in all dogs. No pupil response was noted in six of twelve dogs (IV) for up to 1.5 hours; decreased transient pupillary light reflex was seen for up to 60 minutes in two of twelve dogs (IM). Vomiting was seen in one of twelve dogs. First and second degree AV blocks were observed in one of twelve dogs. Elevated concentrations of ALT were observed in 3 of 12 dogs, without histological changes to the liver.
Dexmedetomidine demonstrated dose dependent effects related to its pharmacology when administered IV or IM to healthy dogs at doses up to five times the recommended dose.

Canine safety study with an anticholinergic

In another laboratory safety study, one of three doses of an IM anticholinergic drug or saline was administered 10 minutes before, at the same time, or 15 minutes after 500 mcg/m^2 IM dexmedetomidine. The anticholinergic drug was given for the prevention or treatment of dexmedetomidine-induced reduction in heart rate. In a crossover design, 18 dogs were used in a total of 72 trials, to evaluate the safety of dexmedetomidine used with an anticholinergic drug.

Dogs were instrumented for the accumulation of continuous ECG data. The following arrhythmias were recorded during the study (some dogs experienced more than one arrhythmia).

Table 8: Arrhythmias recorded during the canine laboratory safety study
Type of arrhythmia | Number of dogs (of 18)
Second degree AV block | 18
Supraventricular tachycardia (SVT) or SVPCs | 16
Ventricular escape beats | 16
Ventricular premature contractions | 14
Third degree AV block | 6
Idioventricular rhythm | 1
Paroxysmal VT | 1
Ventricular bigeminy; SVPCs; pulse alternans | 1
Junctional escape beat | 1

The occurrence of arrhythmias was not related to the presence or absence of the anticholinergic drug. Arrhythmias were transient (although frequent over time in some dogs), returning toward baseline levels within 55 minutes after dexmedetomidine. No dogs required treatment related to these arrhythmias, and none of these arrhythmias persisted or adversely affected the overall clinical status of any dog in the study.

Dexmedetomidine without anticholinergic: Without the anticholinergic drug, and in addition to arrhythmias, dexmedetomidine produced clinically relevant sedation accompanied by a statistically significant reduction in heart rate, respiratory rate, cardiac output, pulmonary arterial temperature, and mixed venous oxygen tension. A statistically significant increase in arterial blood pressure, pulmonary capillary wedge pressure, central venous pressure, and systemic vascular resistance was noted. No dogs experienced hypotension. Dexmedetomidine tended to increase pulmonary vascular resistance. Dexmedetomidine alone had no statistically significant effect on mean pulmonary arterial pressure, arterial pH, arterial carbon dioxide tension, and arterial oxygen tension.
Dexmedetomidine plus anticholinergic: Either of the two higher anticholinergic doses was effective in the prevention or treatment of the dexmedetomidine-induced reduction in heart rate. Anticholinergic (higher doses) given after dexmedetomidine caused marked increases in the occurrence of various cardiac arrhythmias, especially second degree AV block. When the higher doses of anticholinergic drug were given at the same time or 15 minutes after dexmedetomidine, large increases in heart rate (p<0.01) and blood pressure (p<0.05) were seen. Increases were dose related; the highest anticholinergic dose elicited more frequent arrhythmias and larger increases in heart rate and blood pressure.
In conclusion, moderate doses of anticholinergic drug given prior to dexmedetomidine performed best for the prevention of dexmedetomidine-induced reduction of heart rate in dogs. The routine use of anticholinergics given simultaneously with, or after dexmedetomidine, is not recommended.

Feline safety study

In a multiple dose safety study, DEXDOMITOR was administered intramuscularly (IM) at 1×, 3×, and 5× (40, 120, and 200 mcg/kg) the recommended dose of 40 mcg/kg on 3 consecutive days to healthy cats, 6 to 8 months old. A control group received the product vehicle as a placebo (0×). No mortality was observed. The depth and duration of sedation was dose dependent, lasting approximately 2 hours in the 1× group, 2 to 4 hours in the 3× group, and greater than 8 hours in the 5× group. The lowest recorded individual heart rate was 60 beats/minute and occurred in the 5× dose group (2 cats). Cardiac arrhythmias characterized by isolated junctional escape complexes with episodes of junctional escape rhythm were observed during periods of low heart rate or following sinus pauses in all dexmedetomidine dose groups. In most cases the arrhythmia was no longer observed after 1 to 2 hours. Atrioventricular block was not observed. Incidences of arrhythmias were not related to dose; however, more cats were affected by cardiac arrhythmias on the third day of treatment, compared to the first two days of the study. The decrease in respiratory rate, but not the duration, was dose dependent. The rectal temperature decreased in all dexmedetomidine-treated groups, with the lowest temperatures in the 5× group at 8 hours on all three days. Two cats vomited (40 and 120 mcg/kg). Corneal opacity was noted in all dexmedetomidine-dose groups, was transient, related to dose and duration of sedation, and was attributed to lack of lubrication with decreased blinking during sedation. Hematology and blood chemistry were unaffected by treatment. Injection site tolerance was good, with mild inflammatory lesions representative of the IM injection procedure. Gross and histological examination of all other tissues did not reveal any abnormalities related to DEXDOMITOR administration.

Dexmedetomidine demonstrated dose dependent effects related to its pharmacology when administered IM to healthy cats at doses up to five times the recommended dose.

Feline acute tolerance study

IM DEXDOMITOR was administered once at 10X (400 mcg/kg) the recommended dose of 40 mcg/kg to 3 female and 3 male 7 month old cats. No mortality was observed. Sedation was observed within 15 minutes of dosing and lasted for at least 4 hours with full recovery noted between 8 and 24 hours after dosing. Transient observations of corneal dehydration and opacity, miosis, pale skin and gingiva, salivation, and watery ocular discharge were observed in some animals. Vomiting was observed 7 to 11 hours after dosing in all but one animal. Decreases in heart rate accompanied by prolonged PQ and QT intervals were most pronounced 2 to 4 hours after dosing. No atrioventricular (AV) blocks or escape rhythms were noted. In one cat, incidental and reversible premature junctional complexes were seen at 1 and 2 hours after dosing which were considered secondary to bradycardia. Slightly lower respiratory rate and reduced rectal temperature were observed 4 to 8 hours after dosing. Observations had returned to normal by 24 hours after dosing. Mild inflammatory lesions observed histologically at the injection site were representative of the IM injection procedure. No treatment related changes were observed in hematology. Mild elevations in some clinical ALT, AST, and CK, were observed 24 hours after dosing, with a trend towards recovery by 48 hours. Total protein, albumin and globulin levels were slightly lowered in one cat 48 hours after dosing.

STORAGE INFORMATION

Store at controlled room temperature 15-30°C (59-86°F). Protect from freezing. In use shelf life: 90 days at 25°C (77°F).

HOW SUPPLIED

DEXDOMITOR 0.5 mg/mL is supplied in 10-mL, multidose vials containing 0.5 mg of dexmedetomidine hydrochloride per mL.

REFERENCES

(1) Ko JCH, Fox SMF, Mandsager RE. Effects of preemptive atropine administration on incidence of medetomidine-induced bradycardia in dogs. J Am Vet Med Assoc 2001; 218:52-58.
(2) Alibhai HIK, Clarke KW, Lee YH, et al. Cardiopulmonary effects of combinations of medetomidine hydrochloride and atropine sulphate in dogs. Vet Rec 1996; 138:11-13.
(3) Short, CE. Effects of anticholinergic treatment on the cardiac and respiratory systems in dogs sedated with medetomidine. Vet Rec 1991; 129:310-313.
(4) Hikasa Y, Akiba T, Iino Y et al. Cen tral alpha-adrenoceptor subtypes involved in the emetic pathway in cats. Eur J Pharmacol 1992; 229:241-251.

U.S. Patent No. 4,910,214
DEXDOMITOR® is a trademark of Orion Corporation.

Approved by FDA under NADA # 141-267

Mfd by:
Orion Pharma
Orion Corporation
Espoo, Finland
Dist by:
zoetis
Zoetis Inc.
Kalamazoo, MI 49007
Revised: December 2022
144440-3
122691-7